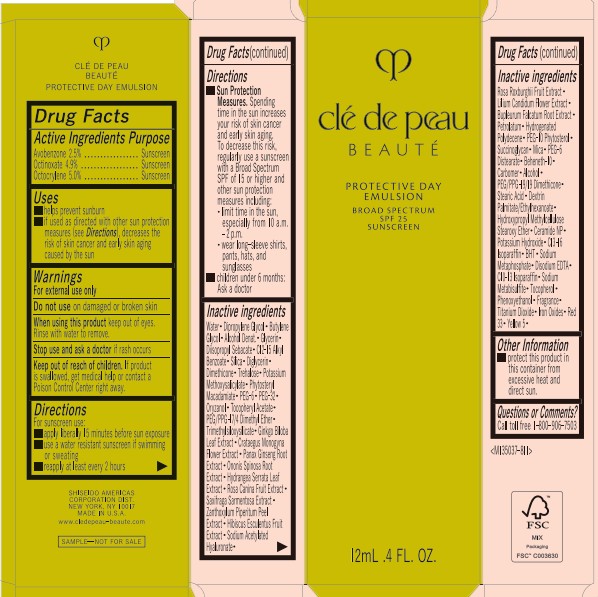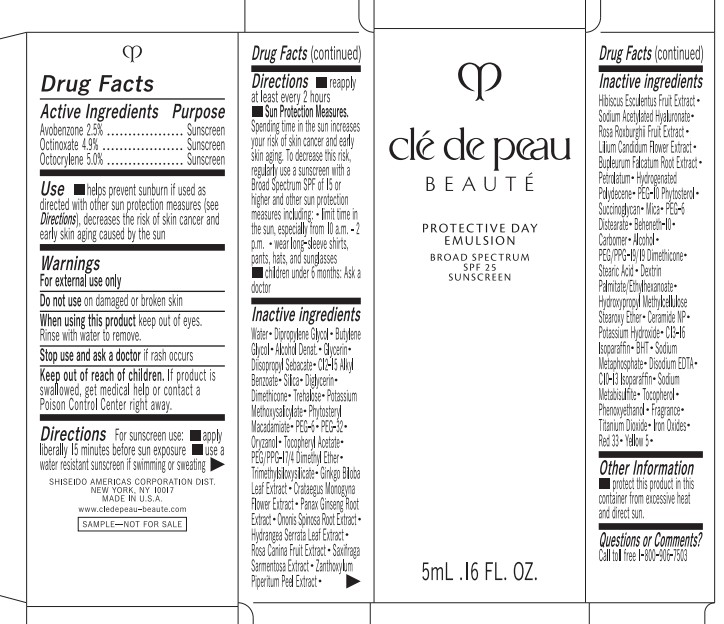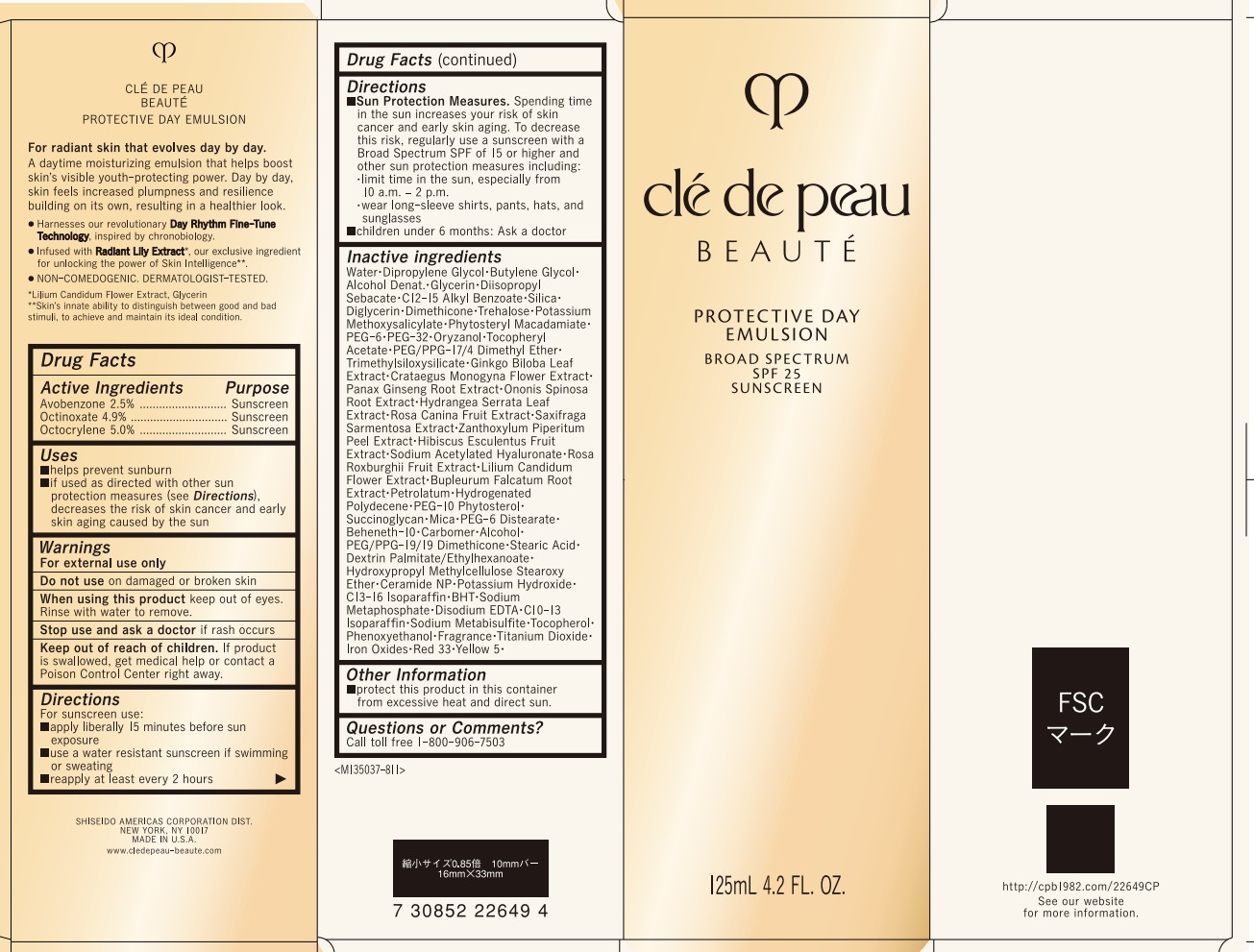 DRUG LABEL: cle de peau BEAUTE Protective Day
NDC: 58411-953 | Form: EMULSION
Manufacturer: Shiseido Americas Corporation
Category: otc | Type: HUMAN OTC DRUG LABEL
Date: 20260225

ACTIVE INGREDIENTS: AVOBENZONE 3.25 g/125 mL; OCTINOXATE 6.38 g/125 mL; OCTOCRYLENE 6.51 g/125 mL
INACTIVE INGREDIENTS: WATER; DIPROPYLENE GLYCOL; BUTYLENE GLYCOL; GLYCERIN; DIISOPROPYL SEBACATE; C12-15 ALKYL BENZOATE; SILICA; DIGLYCERIN; DIMETHICONE; TREHALOSE; POTASSIUM METHOXYSALICYLATE; PHYTOSTERYL MACADAMIATE; PEG-6; PEG-32; ORYZANOL; .ALPHA.-TOCOPHEROL ACETATE; PEG/PPG-17/4 DIMETHYL ETHER; TRIMETHYLSILOXYSILICATE (M/Q 0.6-0.8); GINKGO BILOBA LEAF OIL; CRATAEGUS MONOGYNA FLOWER; PANAX GINSENG ROOT; ONONIS SPINOSA ROOT; HYDRANGEA SERRATA LEAF; ROSA CANINA FRUIT; SAXIFRAGA STOLONIFERA LEAF; ZANTHOXYLUM PIPERITUM FRUIT RIND; HIBISCUS ESCULENTUS SEED EXTRACT; SODIUM ACETYLATED HYALURONATE; ROSA ROXBURGHII FRUIT; LILIUM CANDIDUM FLOWER; BUPLEURUM FALCATUM ROOT; PETROLATUM; HYDROGENATED POLYDECENE (1500 CST); SUCCINOGLYCAN (AGROBACTERIUM TUMEFACIENS); MICA; PEG-6 DISTEARATE; BEHENETH-10; CARBOMER; ALCOHOL; PEG/PPG-19/19 DIMETHICONE; STEARIC ACID; CERAMIDE NP; POTASSIUM HYDROXIDE; C13-16 ISOPARAFFIN; BUTYLATED HYDROXYTOLUENE; SODIUM METAPHOSPHATE; TOCOPHEROL; PHENOXYETHANOL; TITANIUM DIOXIDE; FERRIC OXIDE RED; D&C RED NO. 33; FD&C YELLOW NO. 5

cle de peau BEAUTE Protective Day

Drug Facts

Drug Facts | Purpose
Avobenzone 2.5% | Sunscreen
Octinoxate 4.9% | Sunscreen
Octocrylene 5.0% | Sunscreen

INDICATIONS AND USAGE

- helps prevent sunburn
- if used as directed with other sun protection measures (see Directions) decreases the risk of skin cancer and early skin aging caused by the sun

Warnings

For external use only

Do not use on damaged or broken skin

When using this product keep out of eyes. Rinse with water to remove

Stop use and ask a doctor if rash occurs

Keep out of reach of children. If product is swallowed, get medical help or contact a Poison Control Center right away.

DOSAGE AND ADMINISTRATION

For sunscreen use:

- apply liberally 15 minutes before sun exposure
- use a water resistant sunscreen if swimming or sweating
- reapply at least every 2 hours
- Sun Protection Measures. Spending time in the sun increases your risk of skin cancer and early skin aging. To decrease this risk, regularly use a sunscreen with a Broad Spectrum SPF of 15 or higher and other sun protection measures including:

• limit time in the sun, especially from 10 a.m. - 2 p.m.

• wear long-sleeve shirts, pants, hats, and sunglasses

- children under 6 months: Ask a doctor

INACTIVE INGREDIENT

WATER･DIPROPYLENE GLYCOL･BUTYLENE GLYCOL･ALCOHOL DENAT.･GLYCERIN･DIISOPROPYL SEBACATE･C12-15 ALKYL BENZOATE･SILICA･DIGLYCERIN･DIMETHICONE･TREHALOSE･POTASSIUM METHOXYSALICYLATE･PHYTOSTERYL MACADAMIATE･PEG-6･PEG-32･ORYZANOL･TOCOPHERYL ACETATE･PEG/PPG-17/4 DIMETHYL ETHER･TRIMETHYLSILOXYSILICATE･GINKGO BILOBA LEAF EXTRACT･CRATAEGUS MONOGYNA FLOWER EXTRACT･PANAX GINSENG ROOT EXTRACT･ONONIS SPINOSA ROOT EXTRACT･HYDRANGEA SERRATA LEAF EXTRACT･ROSA CANINA FRUIT EXTRACT･SAXIFRAGA SARMENTOSA EXTRACT･ZANTHOXYLUM PIPERITUM PEEL EXTRACT･HIBISCUS ESCULENTUS FRUIT EXTRACT･SODIUM ACETYLATED HYALURONATE･ROSA ROXBURGHII FRUIT EXTRACT･LILIUM CANDIDUM FLOWER EXTRACT･BUPLEURUM FALCATUM ROOT EXTRACT･PETROLATUM･HYDROGENATED POLYDECENE･PEG-10 PHYTOSTEROL･SUCCINOGLYCAN･MICA･PEG-6 DISTEARATE･BEHENETH-10･CARBOMER･ALCOHOL･PEG/PPG-19/19 DIMETHICONE･STEARIC ACID･DEXTRIN PALMITATE/ETHYLHEXANOATE･HYDROXYPROPYL METHYLCELLULOSE STEAROXY ETHER･CERAMIDE NP･POTASSIUM HYDROXIDE･C13-16 ISOPARAFFIN･BHT･SODIUM METAPHOSPHATE･DISODIUM EDTA･C10-13 ISOPARAFFIN･SODIUM METABISULFITE･TOCOPHEROL･PHENOXYETHANOL･FRAGRANCE･TITANIUM DIOXIDE･IRON OXIDES･RED 33･YELLOW 5･

Other Information

- protect this product in this container from excessive heat and direct sunlight

Questions or Comments?

Call toll free 1-800-906-7503

PRINCIPAL DISPLAY PANEL - 125 mL Bottle Carton

clé de peau

BEAUTÉ

PROTECTIVE DAY

EMULSION

BROAD SPECTRUM

SPF 25

SUNSCREEN

125mL 4.2 FL. OZ.

PRINCIPAL DISPLAY PANEL - 12 mL Bottle Carton

clé de peau

BEAUTÉ

PROTECTIVE DAY

EMULSION

BROAD SPECTRUM

SPF 25

SUNSCREEN

PRINCIPAL DISPLAY PANEL - 5 mL Bottle Carton

clé de peau

BEAUTÉ

PROTECTIVE DAY

EMULSION

BROAD SPECTRUM

SPF 25

SUNSCREEN